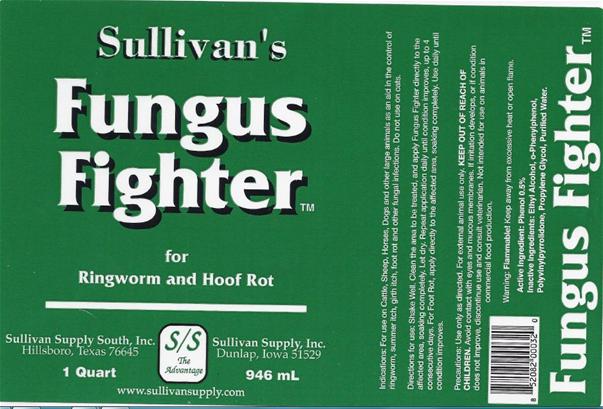 DRUG LABEL: Fungus Fighte
NDC: 42417-017 | Form: LIQUID
Manufacturer: Sullivan Supply, Inc.
Category: animal | Type: OTC ANIMAL DRUG LABEL
Date: 20120615

ACTIVE INGREDIENTS: PHENOL 5.000 g/1.161 L
INACTIVE INGREDIENTS: ALCOHOL 793.000 g/1.161 L

Fungus Fighter

Indications:

For use on Cattle, Sheep, Horses, Dogs and other large animals as an aid in the control of ringworm, summer itch, foot rot and other fungal infections. Do not use on cats.

Directions for Use:

Shake Well. Clean the area to be treated, and apply Fungus Fighter directly to the affected area, soaking completely. Let dry. Repeat application daily until condition improves, up to 4 consecutive days. For Foot Rot, apply directly to the affected area, soaking completely. Use daily until condition improves.

Precautions:

Use only as directed. For external animal use only. Avoid contact with eyes and mucous membranes. If irritation develops, or if condition does not improve, discontinue use and consult veterinarian. Not intended for use on animals in commercial food production.

Warning:

Flammable! Keep away from excessive heat or open flame.

Use

for Ringworm and Hoof Rot

Active Ingredient:

Phenol 0.5%

Inactive Ingredients:

Ethyl Alcohol, o-Phenylphenol, Polyvinylpyrrolidone, Propylene Glycol, Purified Water

Principle Display Panel

1 Quart Label

1 Quart Label